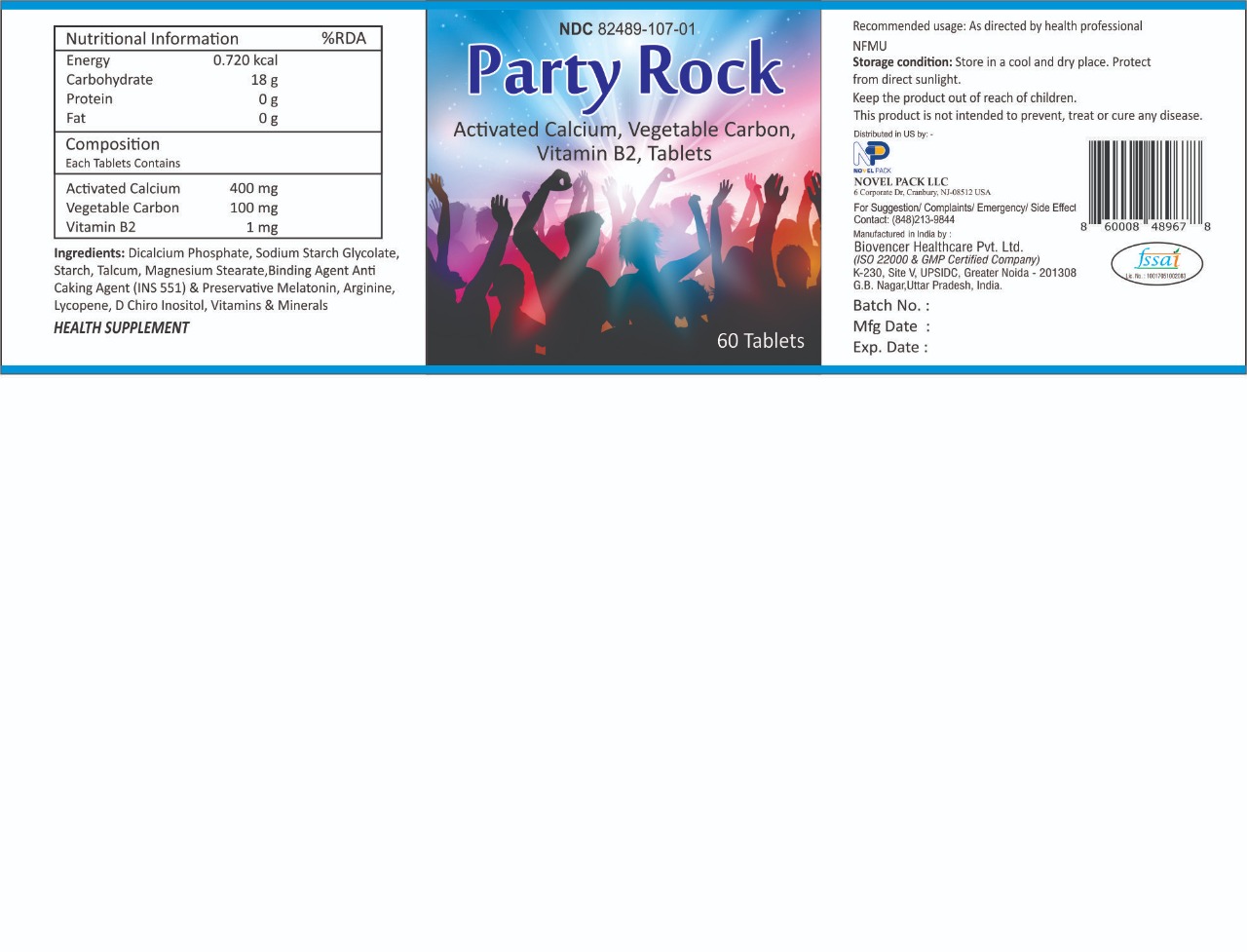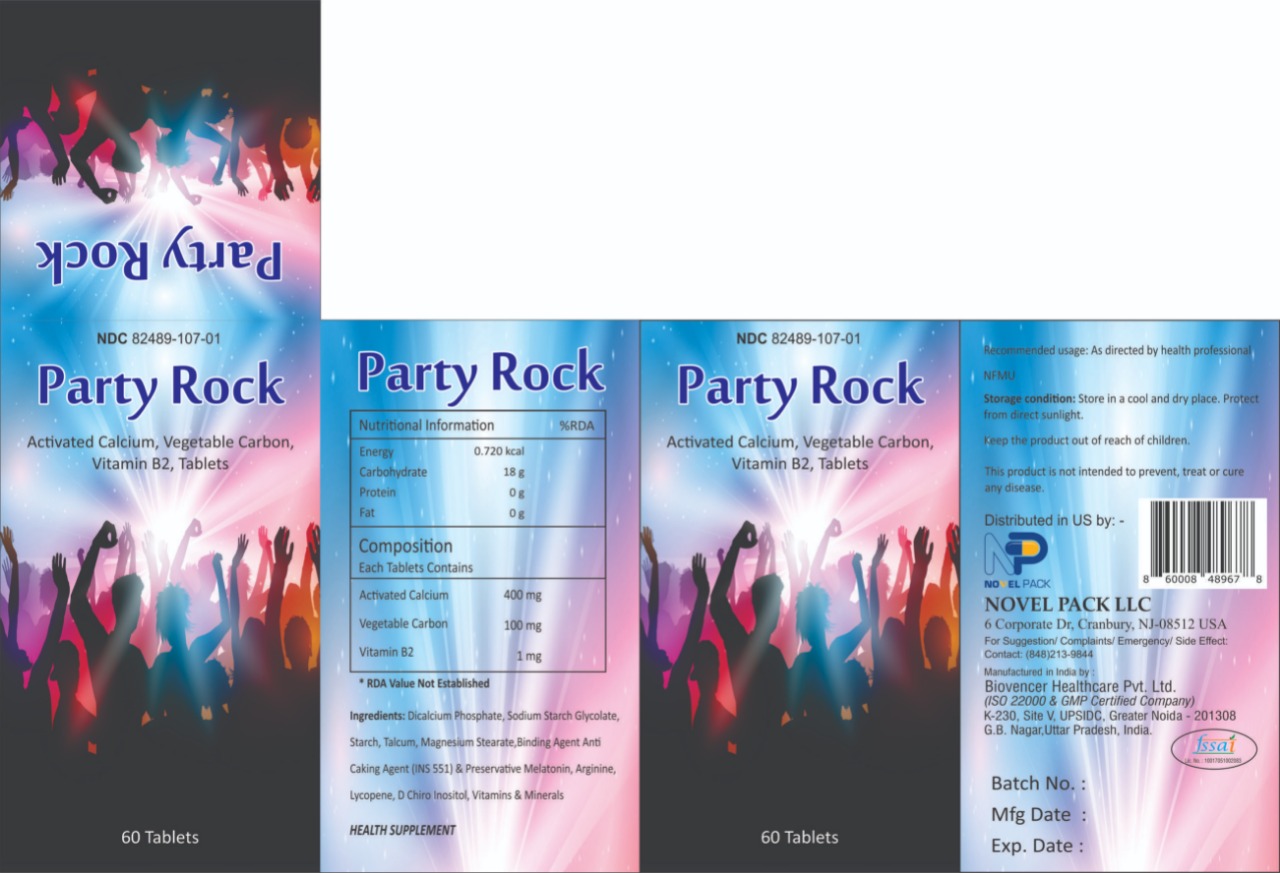 DRUG LABEL: Party Rock
NDC: 82489-107 | Form: TABLET
Manufacturer: NOVEL PACK LLC
Category: other | Type: DIETARY SUPPLEMENT
Date: 20220430

ACTIVE INGREDIENTS: CALCIUM 400 mg/1 1; CARBON ION 100 mg/1 1; RIBOFLAVIN 1 mg/1 1
INACTIVE INGREDIENTS: CALCIUM PHOSPHATE, DIBASIC, DIHYDRATE; SODIUM STARCH GLYCOLATE TYPE A; STARCH, CORN; MAGNESIUM STEARATE; TALC; MELATONIN; ARGININE; LYCOPENE; INOSITOL

Party Rock
Activated Calcium, Vegetable Carbon, Vitamin B2 Tablets

STATEMENT OF IDENTITY

Party Rock
Activated Calcium, Vegetable Carbon, Vitamin B2 Tablets

Storage Condition

Store in a cool and dry place. Protect from direct sunlight

Recommended Usuage

As directed by Health professional